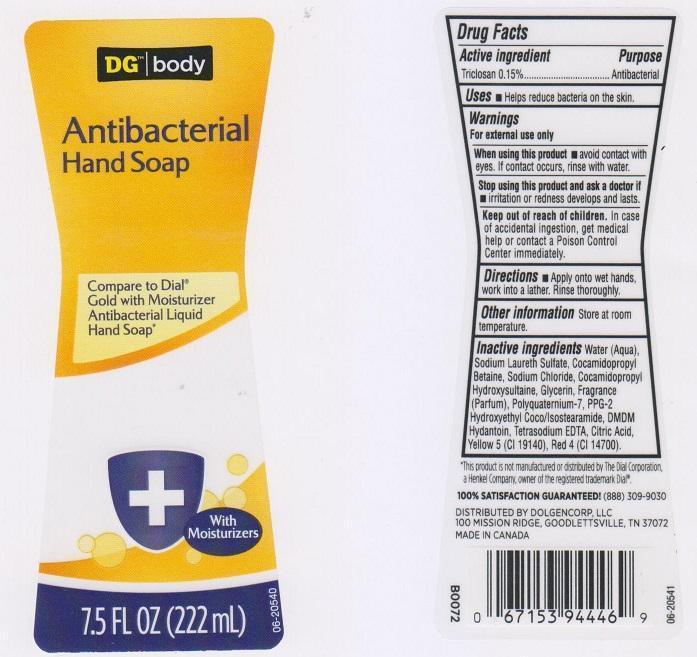 DRUG LABEL: DG BODY
NDC: 55910-294 | Form: SOAP
Manufacturer: DOLGENCORP INC
Category: otc | Type: HUMAN OTC DRUG LABEL
Date: 20150827

ACTIVE INGREDIENTS: TRICLOSAN 1.5 mg/1 mL
INACTIVE INGREDIENTS: WATER; SODIUM LAURETH SULFATE; COCAMIDOPROPYL BETAINE; SODIUM CHLORIDE; COCAMIDOPROPYL HYDROXYSULTAINE; GLYCERIN; POLYQUATERNIUM-7 (70/30 ACRYLAMIDE/DADMAC; 1600000 MW); PPG-2 HYDROXYETHYL COCO/ISOSTEARAMIDE; DMDM HYDANTOIN; EDETATE SODIUM; CITRIC ACID MONOHYDRATE; FD&C YELLOW NO. 5; FD&C RED NO. 4

DRUG FACTS

Active ingredient

Triclosan 0.15%

Purpose

Antibacterial

Uses

Helps reduce bacteria on the skin

Warnings

For external use only

When using this product

avoid contact with eyes. If contact occurs, rinse with water

Stop using this product and ask a doctor if

irritation or redness develops and lasts.

Keep out of reach of children.

In case of accidental ingestion, get medical help or contact a Poison Control Center immediately.

Directions

Apply onto wet hands, work into a lather. Rinse thoroughly

Other information

Store at room temperature

Inactive ingredients

Water (Aqua), Sodium Laureth Sulfate, Cocamidopropyl Betaine, Sodium Chloride, Cocamidopropyl Hydroxysultaine, Glycerin, Fragrance (Parfum), Polyquaternium-7, PPG-2 Hydroxyethyl Coco/Isostearamide, DMDM Hydantoin, Tetrasodium EDTA, Citric Acid, Yellow 5 (CI 19140), Red 4 (CI 14700)